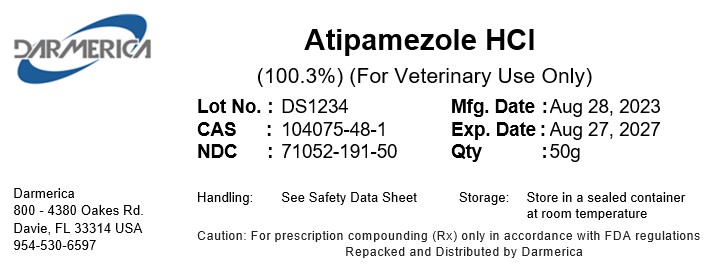 DRUG LABEL: Atipamezole HCl
NDC: 71052-191 | Form: POWDER
Manufacturer: DARMERICA, LLC
Category: other | Type: BULK INGREDIENT - ANIMAL DRUG
Date: 20260105

ACTIVE INGREDIENTS: ATIPAMEZOLE HYDROCHLORIDE 1 g/1 g

Atipamezole HCl